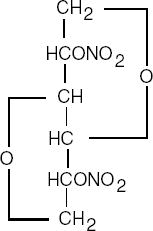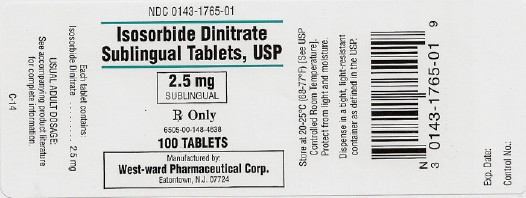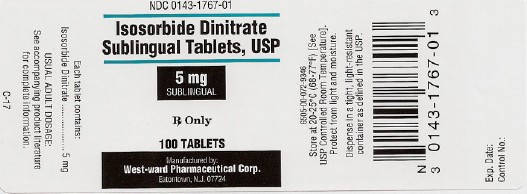 DRUG LABEL: Isosorbide Dinitrate
NDC: 0143-1765 | Form: TABLET
Manufacturer: West-ward Pharmaceutical Corp
Category: prescription | Type: HUMAN PRESCRIPTION DRUG LABEL
Date: 20120518

ACTIVE INGREDIENTS: ISOSORBIDE DINITRATE 2.5 mg/1 1
INACTIVE INGREDIENTS: AMMONIUM PHOSPHATE, DIBASIC; ANHYDROUS LACTOSE; SILICON DIOXIDE; STARCH, CORN; D&C YELLOW NO. 10; FD&C YELLOW NO. 6; MAGNESIUM STEARATE; CELLULOSE, MICROCRYSTALLINE; SODIUM STARCH GLYCOLATE TYPE A POTATO

ISOSORBIDE DINITRATE SUBLINGUAL TABLETS, USP

Rev 11/07

Rx Only

DESCRIPTION

Isosorbide dinitrate (ISDN) is 1,4:3,6-dianhydro-D-glucitol 2,5-dinitrate, an organic nitrate whose structural formula is:

and whose molecular weight is 236.14. The organic nitrates are vasodilators, active on both arteries and veins.

ISDN is a white, crystalline, odorless compound which is stable in air and in solution, has a melting point of 70°C and has an optical rotation of +134° (c=1.0, alcohol. 20°C). ISDN is freely soluble in organic solvents such as acetone, alcohol, and ether, but is only sparingly soluble in water.

Each isosorbide dinitrate sublingual tablet contains 2.5 mg or 5 mg of ISDN.

Inactive ingredients are as follows:

2.5 mg Sublingual: Ammonium phosphate dibasic, anhydrous lactose, colloidal silicon dioxide, corn starch, D&C Yellow No. 10 Lake, FD&C Yellow No. 6 Lake, magnesium stearate, microcrystalline cellulose, sodium starch glycolate.

5 mg Sublingual: Ammonium phosphate dibasic, anhydrous lactose, colloidal silicon dioxide, corn starch, magnesium stearate, microcrystalline cellulose.

CLINICAL PHARMACOLOGY

The principal pharmacological action of ISDN is relaxation of vascular smooth muscle and consequent dilatation of peripheral arteries and veins, especially the latter. Dilatation of the veins promotes peripheral pooling of blood and decreases venous return to the heart, thereby reducing left ventricular end-diastolic pressure and pulmonary capillary wedge pressure (preload). Arteriolar relaxation reduces systemic vascular lesistance, systolic arterial pressure, and mean arterial pressure (afterload). Dilatation of the coronary arteries also occurs. The relative importance of preload reduction, afterload reduction, and coronary dilatation remains undefined.

Dosing regimens for most chronically used drugs are designed to provide plasma concentrations that are continuously greater than a minimally effective concentration. This strategy is inappropriate for organic nitrates. Several well-controlled clinical trials have used exercise testing to assess the anti-anginal efficacy of continuously-delivered nitrates. In the large majority of these trials, active agents were no more effective than placebo after 24 hours (or less) of continuous therapy. Attempts to overcome nitrate tolerance by dose escalation, even to doses far in excess of those used acutely, have consistently failed. Only after nitrates have been absent from the body for several hours has their anti-anginal efficacy been restored.

Pharmacokinetics

Bioavailability of ISDN after single sublingual doses is 40 to 50%. Multiple-dose studies of sublingual ISDN pharmacokinetics have not been reported; multiple-dose studies of ingested ISDN have observed progressive increases in bioavailability during chronic therapy. Serum levels of ISDN reach their maxima 10 to 15 minutes after sublingual dosing.

Once absorbed, the distribution volume of ISDN is 2 to 4 L/kg, and this volume is cleared at the rate of 2 to 4 L/min, so ISDN's half-life in serum is about an hour. Since the clearance exceeds hepatic blood flow, considerable extrahepatic metabolism must also occur. Clearance is affected primarily by denitration to the 2-mononitrate (15 to 25%) and the 5-mononitrate (75 to 85%).

Both metabolites have biological activity, especially the 5-mononitrate. With an overall half-life of about 5 hours, the 5-mononitrate is cleared from the serum by denitration to isosorbide; glucuronidation to the 5-mononitrate glucuronide; and denitration/hydration to sorbitol. The 2-mononitrate has been less well studied, but it appears to participate in the same metabolic pathways, with a half-life of about 2 hours.

The daily dose-free interval sufficient to avoid tolerance to organic nitrates has not been well defined. Studies of nitroglycerin (an organic nitrate with a very short half-life) have shown that daily dose-free intervals of 10 to 12 hours are usually sufficient to minimize tolerance. Daily dose-free intervals that have succeeded in avoiding tolerance during trials of moderate doses (e.g., 30 mg) of immediate-release ISDN have generally been somewhat longer (at least 14 hours), but this is consistent with the longer half-lives of ISDN and its active metabolites.

Few well-controlled clinical trials of organic nitrates have been designed to detect rebound or withdrawal effects. In one such trial, however, subjects receiving nitroglycerin had less exercise tolerance at the end of the daily dose-fiee interval than the parallel group receiving placebo. The incidence, magnitude, and clinical significance of similar phenomena in patients receiving ISDN have not been studied.

Clinical trials

In a controlled trial in which 0.4 mg of sublingual nitroglycerin took 1.9 minutes to begin to produce an anti-anginal effect, 5 mg of sublingual ISDN took 3.4 minutes to begin to produce a similar effect. In the same trial, the anti-anginal effect of the sublingual nitroglycerin was evident for about an hour, while that of the sublingual ISDN lasted about 2 hours.

In other controlled trials, the anti-anginal efficacy of sublingual ISDN has persisted for periods ranging from 30 minutes up to 4 hours.

Multiple-dose trials of sublingual ISDN have not been reported. Multiple-dose trials of ingested formulations of ISDN have shown that ISDN's anti-anginal efficacy is substantially attenuated by tolerance unless the daily regimen includes a dose-free interval of at least 14 hours. The daily dose-free interval necessary in any chronic regimen using sublingual ISDN is not known.

From large, well-controlled studies of other nitrates, it is reasonable to believe that the maximal achievable daily duration of anti-anginal effect from ISDN is about 12 hours. No dosing regimen for ISDN has, however, ever actually been shown to achieve this duration of effect. In the absence of data from multiple-dose trials, and considering the capacity of organic nitrates to induce tolerance, it is not reasonable to assume that multiple sublingual ISDN tablets taken during the course of a day will all have similar effects.

INDICATIONS AND USAGE

Isosorbide dinitrate sublingual tablets are indicated for the prevention and treatment of angina pectoris due to coronary artery disease. However, because the onset of action of sublingual ISDN is significantly slower than that of sublingual nitroglycerin, sublingual ISDN is not the drug of first choice for abortion of an acute anginal episode.

CONTRAINDICATIONS

Allergic reactions to organic nitrates are extremely rare, but they do occur. The isosorbide dinitrate sublingual tablet is contraindicated in patients who are allergic to ISDN or any of its other ingredients.

WARNINGS

Amplification of the vasodilatory effects of isosorbide dinitrate by sildenafil can result in severe hypotension. The time course and dose dependence of this interaction have not been studied. Appropriate supportive care has not been studied, but it seems reasonable to treat this as a nitrate overdose, with elevation of the extremities and with central volume expansion.

The benefits of sublingual ISDN in patients with acute myocardial infarction or congestive heart failure have not been established. If one elects to use ISDN in these conditions, careful clinical or hemodynamic monitoring must be used to avoid the hazards of hypotension and tachycardia.

PRECAUTIONS

General

Severe hypotension, particularly with upright posture, may occur with even small doses of ISDN. This drug should therefore be used with caution in patients who may be volume depleted or who, for whatever reason, are already hypotensive. Hypotension induced by ISDN may be accompanied by paradoxical bradycardia and increased angina pectoris.

Nitrate therapy may aggravate the angina caused by hypertrophic cardiomyopathy.

As tolerance to ISDN develops, the effect of sublingual nitroglycerin on exercise tolerance, although still observable, is somewhat blunted.

Some clinical trials in angina patients have provided nitroglycerin for about 12 continuous hours of every 24-hour day. During the daily dose-free interval in some of these trials, anginal attacks have been more easily provoked than before treatment, and patients have demonstrated hemodynamic rebound and decreased exercise tolerance. The importance of these observations to the routine, clinical use of sublingual ISDN is not known.

In industrial workers who have had long-term exposure to unknown (presumably high) doses of organic nitrates, tolerance clearly occurs. Chest pain, acute myocardial infarction, and even sudden death have occurred during temporary withdrawal of nitrates from these workers, demonstrating the existence of true physical dependence.

Information for Patients

Patients should be told that the anti-anginal efficacy of ISDN is strongly related to its dosing regimen, so the prescribed schedule of dosing should be followed carefully. In particular, daily headaches sometimes accompany treatment with ISDN. In patients who get these headaches, the headaches are a marker of the activity of the drug. Patients should resist the temptation to avoid headaches by altering the schedule of their treatment with ISDN, since loss of headache may be associated with simultaneous loss of anti-anginal efficacy. Aspirin and/or acetaminophen, on the other hand, often successfully relieve ISDN-induced headaches with no deleterious effect on ISDN'S anti-anginal efficacy.

Treatment with ISDN may be associated with lightheadedness on standing, especially just after rising from a recumbent or seated position. This effect may be more frequent in patients who have also consumed alcohol.

Drug Interactions

The vasodilating effects of ISDN may be additive with those of other vasodilators. Alcohol, in particular, has been found to exhibit additive effects of this variety.

Carcinogenesis. Mutagenesis. Impairment of Fertility

No long-term studies in animals have been performed to evaluate the carcinogenic potential of ISDN. In a modified two-litter reproduction study, there was no remarkable gross pathology and no altered fertility or gestation among rats fed ISDN at 25 or 100 mg/kg/day.

Pregnancy Category C

At oral doses 35 and 150 times the maximum recommended human daily dose. ISDN has been shown to cause a dose-related increase in embryotoxicity (increase in mummified pups) in rabbits. There are no adequate, well-controlled studies in pregnant women. ISDN should be used during pregnancy only if the potential benefit justifies the potential risk to the fetus.

Nursing Mothers

It is not known whether ISDN is excreted in human milk. Because many drugs are excreted in human milk, caution should be exercised when ISDN is administered to a nursing woman.

Pediatric Use

Safety and effectiveness in pediatric patients have not been established.

Geriatric Use

Clinical studies of sublingual ISDN did not include sufficient numbers of subjects aged 65 and over to determine whether they respond differently from younger subjects. Other reported clinical experience has not identified differences in responses between the elderly and younger patients. In general, dose selection for an elderly patient should be cautious, usually starting at the low end of the dosing range, reflecting the greater frequency of decreased hepatic, renal, or cardiac function, and of concomitant disease or other drug therapy.

ADVERSE REACTIONS

Adverse reactions to ISDN are generally dose-related, and almost all of these reactions are the result of ISDN's activity as a vasodilator. Headache, which may be severe, is the most commonly reported side effect. Headache may be recurrent with each daily dose, especially at higher doses. Transient episodes of lightheadedness, occasionally related to blood pressure changes, may also occur.

Hypotension occurs infrequently, but in some patients it may be severe enough to warrant discontinuation of therapy. Syncope, crescendo angina, and rebound hypertension have been reported but are uncommon.

Extremely rarely, ordinary doses of organic nitrates have caused methemoglobinemia in normal-seeming patients. Methemoglobinemia is so infrequent at these doses that further discussion of its diagnosis and treatment is deferred (see OVERDOSAGE).

Data are not available to allow estimation of the frequency of adverse reactions during treatment of isosorbide dinitrate sublingual tablets.

OVERDOSAGE

Hemodynamic Effects

The ill effects of ISDN overdose are generally the results of ISDN's capacity to induce vasodilatation, venous pooling, reduced cardiac output, and hypotension. These hemodynamic changes may have protean manifestations, including increased intracranial pressure, with any or all of persistent throbbing headache, confusion, and moderate fever; vertigo; palpitations: visual disturbances: nausea and vomiting (possibly with colic and even bloody diarrhea); syncope (especially in the upright posture); air hunger and dyspnea, later followed by reduced ventilatory effort; diaphoresis, with the skin either flushed or cold and clammy; heart block and bradycardia; paralysis; coma; seizures; and death.

Laboratory determinations of serum levels of ISDN and it metabolites are not widely available, and such determinations have, in any event, no established role in the management of ISDN overdose.

There are no data suggesting what dose of ISDN is likely to be life-threatening in humans. In rats, the median acute lethal dose (LD50) was found to be 1100 mg/kg.

No data are available to suggest physiological maneuvers (e.g., maneuvers to change the pH of the urine) that might accelerate elimination of ISDN and its active metabolites. Similarly, it is not known which, if any, of these substances can usefully be removed from the body by hemodialysis.

No specific antagonist to the vasodilator effects of ISDN is known, and no intervention has been subject to controlled studies as a therapy for ISDN overdose. Because the hypotension associated with ISDN overdose is the result of venodilatation and arterial hypovolemia, prudent therapy in this situation should be directed toward increase in central fluid volume. Passive elevation of the patient's legs may be sufficient, but intravenous infusion of normal saline or similar fluid may also be necessary.

The use of epinephrine or other arterial vasoconstrictors in this setting is likely to do more harm than good.

In patients with renal disease or congestive heart failure, therapy resulting in central volume expansion is not without hazard. Treatment of ISDN overdose in these patients may be subtle and difficult, and invasive monitoring may be required.

Methemoglobinemia

Nitrate ions liberated during metabolism of ISDN can oxidize hemoglobin into methemoglobin. Even in patients totally without cytochrome b5 reductase activity, however and even assuming that the nitrate moieties of ISDN are quantitatively applied to oxidation of hemoglobin, about 1 mg/kg of ISDN should be required before any of these patients manifests clinically significant (≥10%) methemoglobinemia. In patients with normal reductase function, significant production of methemoglobin should require even larger doses of ISDN. In one study in which 36 patients received 2 to 4 weeks of continuous nitroglycerin therapy at 3.1 to 4.4 mg/hr (equivalent, in total administered dose of nitrate ions, to 4.8 to 6.9 mg of bioavailable ISDN per hour), the average methemoglobin level measured was 0.2%; this was comparable to that observed in parallel patients who received placebo.

Notwithstanding these observations, there are case reports of significant methemoglobinemia in association with moderate overdoses of organic nitrates. None of the affected patients had been thought to be unusually susceptible.

Methemoglobin levels are available from most clinical laboratories. The diagnosis should be suspected in patients who exhibit signs of impaired oxygen delivery despite adequate cardiac output and adequate arterial pO2. Classically, methemoglobinemic blood is described as chocolate brown, without color change on exposure to air.

When methemoglobinemia is diagnosed, the treatment of choice is methylene blue, 1 to 2 mg/kg intravenously.

DOSAGE AND ADMINISTRATION

As noted under CLINICAL PHARMACOLOGY, multiple studies with ISDN and other nitrates have shown that maintenance of continuous 24-hour plasma levels results in refractory tolerance. Every dosing regimen for ISDN must provide a daily dose-free interval to minimize the development of this tolerance. In the case of sublingual tablets, it is probably true that one of the daily dose-free intervals must be somewhat longer than 14 hours.

As also noted under CLINICAL PHARMACOLOGY, the efficacy of daily doses after the first has never been demonstrated.

Large controlled studies with other nitrates suggest that no dosing regimen with Isosorbide Dinitrate Sublingual Tablets should be expected to provide more than about 12 hours of continuous anti-anginal efficacy per day.

A patient anticipating activity likely to cause angina should take one isosorbide dinitrate sublingual tablet (2.5 to 5 mg) about 15 minutes before the activity is expected to begin. Isosorbide dinitrate sublingual tablets may be used to abort an acute anginal episode, but its use is recommended only in patients who fail to respond to sublingual nitroglycerin.

HOW SUPPLIED

Isosorbide Dinitrate Sublingual Tablets USP 2.5 mg: Yellow, round, compressed tablet imprinted "W1".

- Bottles of 100 tablets.
- Bottles of 1000 tablets.
- Unit Dose Boxes of 100 tablets.

Isosorbide Dinitrate Sublingual Tablets USP 5 mg: White, round, compressed tablet engraved with "W3".

- Bottles of 100 tablets.
- Bottles of 1000 tablets.
- Unit Dose Boxes of 100 tablets.

Dispense in a tight, light-resistant container as defined in the USP using a child-resistant closure.

Store at 20-25°C (68-77°F) [See USP Controlled Room Temperature]. Protect from light and moisture.

Also available: Isosorbide Dinitrate Oral Tablets in the following dosage strengths:

5 mg; in bottles of 100, 500, 1000 or unit dose boxes of 100 tablets.
10 mg; in bottles of 100, 500, 1000 or unit dose boxes of 100 tablets.
20 mg; in bottles of 100, 1000 or unit dose boxes of 100 tablets.

Manufactured by:
West-ward Pharmaceutical Corp.
Eatontown, NJ 07724
Revised November 2007

PRINCIPAL DISPLAY PANEL

Isosorbide Dinitrate Sublingual Tablets, USP
NDC 0143-1765-01
2.5 mg/100 Tablets

PRINCIPAL DISPLAY PANEL

Isosorbide Dinitrate Subligual Tablets, USP
NDC 0143-1767-01
5 mg/100 Tablets